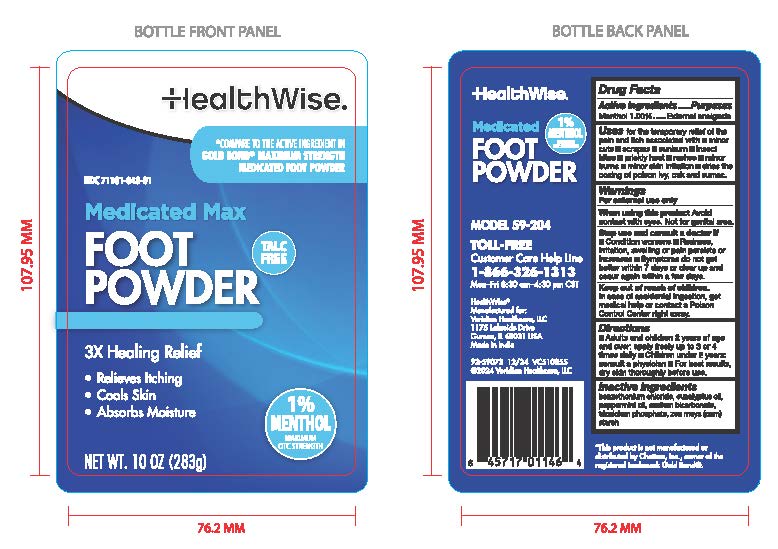 DRUG LABEL: HealthWise Medicated Foot Powder
NDC: 71101-048 | Form: POWDER
Manufacturer: Veridian Healthcare
Category: otc | Type: HUMAN OTC DRUG LABEL
Date: 20241212

ACTIVE INGREDIENTS: MENTHOL 1 g/100 g
INACTIVE INGREDIENTS: SODIUM BICARBONATE; TRICALCIUM PHOSPHATE; BENZETHONIUM CHLORIDE; EUCALYPTUS OIL; PEPPERMINT OIL; STARCH, CORN

HealthWise Medicated Foot Powder 1% Menthol 10 oz

Active Ingredient

Menthol 1%

Purpose

External analgesic

Uses

for the temporary relief of the pain and itch associated with:
■ minor cuts ■ scrapes ■ sunburn ■ insect bites ■ prickly heat ■ rashes ■ minor burns ■ minor skin irritation ■ dries the oozing of poison ivy, oak, and sumac.

Warnings

For external use only

When using this product

Avoid contact with eyes. Not for genital area

Stop use and consult a doctor if

■ Condition worsens ■ Redness, irritation, swelling or pain persists or increases ■ Symptoms do not get better within 7 days or clear up and occur again within a few days.

Keep out of reach of children

In case of accidental ingestion, get medical help or contact a Poison Control Center right away.

Directions

■ Adults and children 2 years of age and over: apply freely up to 3 or 4 times daily ■ Children under 2 years: consult a physician ■ For best results, dry skin thoroughly before use.

Inactive Ingredients

benzethonium chloride, eucalyptus oil, peppermint oil, sodium bicarbonate, tricalcium phospate, zea mays (corn) starch

Questions or comments

Call toll-free 1-866-326-1313